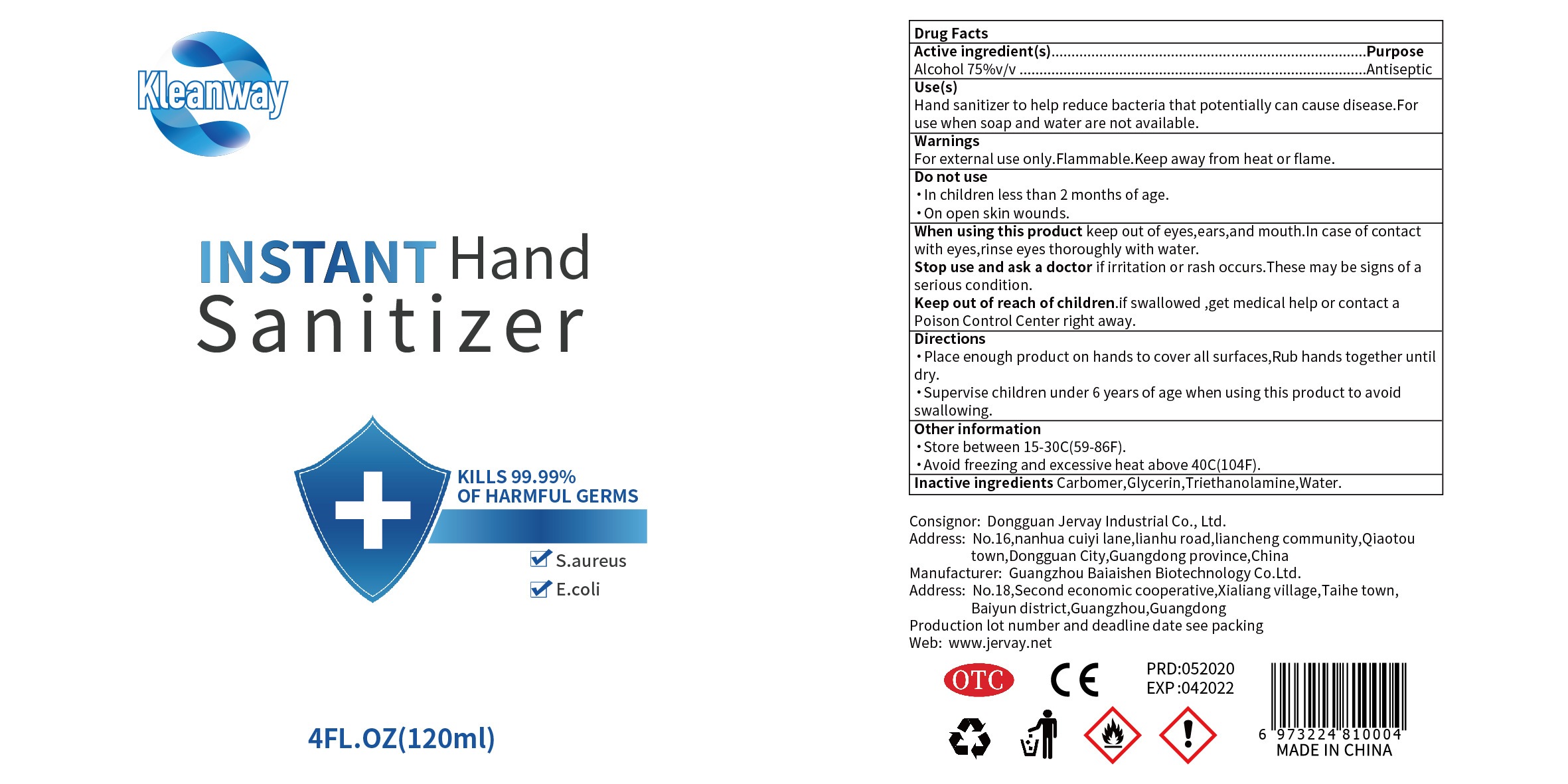 DRUG LABEL: Hand Sanitizer
NDC: 41876-005 | Form: LIQUID
Manufacturer: Dongguan Jervay Industrial Co.,LTD
Category: otc | Type: HUMAN OTC DRUG LABEL
Date: 20220530

ACTIVE INGREDIENTS: ALCOHOL 90 mL/120 mL
INACTIVE INGREDIENTS: GLYCERIN; TROLAMINE; WATER; CARBOMER HOMOPOLYMER, UNSPECIFIED TYPE

DOSAGE AND ADMINISTRATION

Store between 15-30C(59-86F).Avoid freezing and excessive heat above 40C(104F).

INACTIVE INGREDIENT

Carbomer

Glycerol

Triethanolamine

Water

INDICATIONS AND USAGE

Place enough product on hands to cover all surfaces,Rub hands together until dry.

ACTIVE INGREDIENT

Alcohol

keep out of children

PURPOSE

Disinfection
Sterilization

WARNINGS

For external use only.Flammable.Keep away from heat or flame.